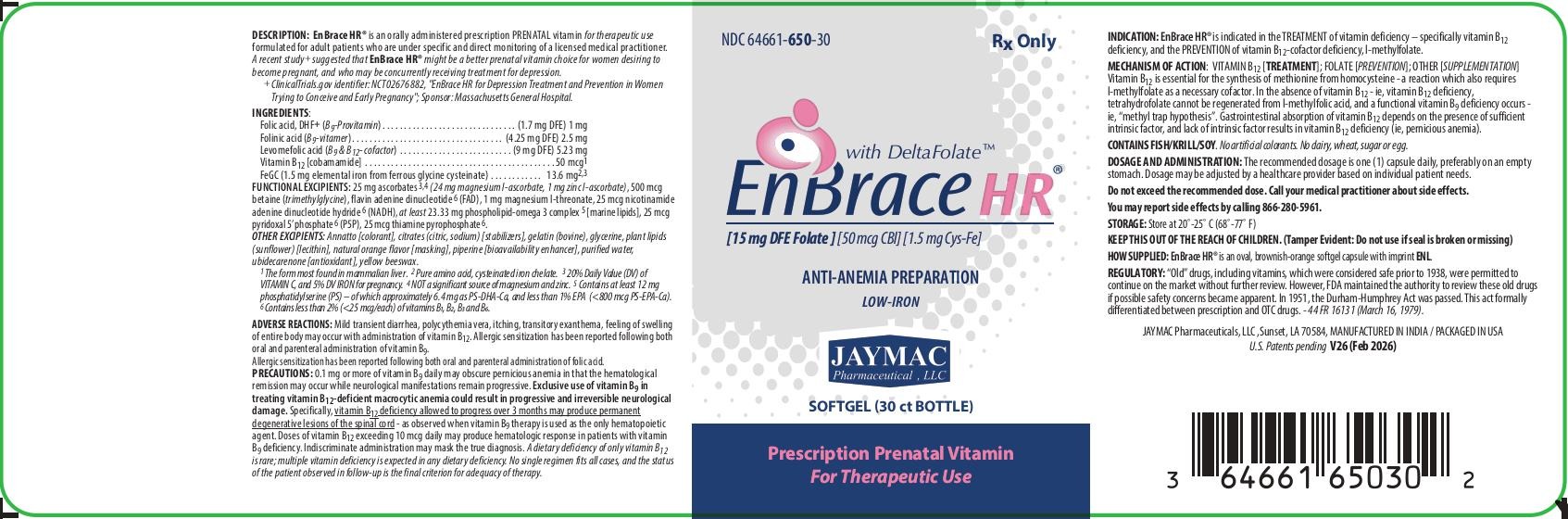 DRUG LABEL: EnBrace HR
NDC: 64661-650 | Form: CAPSULE, DELAYED RELEASE PELLETS
Manufacturer: Jaymac Pharmaceuticals, LLC
Category: prescription | Type: HUMAN PRESCRIPTION DRUG LABEL
Date: 20260210

ACTIVE INGREDIENTS: LEVOMEFOLATE MAGNESIUM 5.23 mg/1 1; LEUCOVORIN 2.5 mg/1 1; FOLIC ACID 1 mg/1 1; FERROUS CYSTEINE GLYCINATE 13.6 mg/1 1; MAGNESIUM ASCORBATE 24 mg/1 1; ZINC ASCORBATE 1 mg/1 1; COCARBOXYLASE 25 ug/1 1; FLAVIN ADENINE DINUCLEOTIDE 25 ug/1 1; NADH 25 ug/1 1; PYRIDOXAL PHOSPHATE ANHYDROUS 25 ug/1 1; COBAMAMIDE 50 ug/1 1; BETAINE 500 ug/1 1; MAGNESIUM L-THREONATE 1 mg/1 1; 1,2-DOCOSAHEXANOYL-SN-GLYCERO-3-PHOSPHOSERINE CALCIUM 6.4 mg/1 1; 1,2-ICOSAPENTOYL-SN-GLYCERO-3-PHOSPHOSERINE CALCIUM 800 ug/1 1; PHOSPHATIDYL SERINE 12 mg/1 1
INACTIVE INGREDIENTS: ANNATTO; GELATIN; LECITHIN, SUNFLOWER; PIPERINE; WATER; UBIDECARENONE; YELLOW WAX

EnBrace HR ®

EnBrace HR®

with DeltaFolate™

[15 mg DFE Folate ] [50 mcg CBl] [1.5 mg Cys-Fe]

ANTI-ANEMIA PREPARATION

Low-IRON

Prescription Prenatal Vitamin For Therapeutic Use

SOFTGEL (30ct bottle)

NDC 64661-650-30

Rx Only

GLUTEN-FREE

DESCRIPTION:

EnBrace HR® is an orally administered prescription prenatal vitamin for therapeutic use formulated for adult patients who are under specific and direct monitoring of a licensed medical practitioner.

EnBrace HR® contains a small amount of iron and may be taken concurrently with iron supplementation.

INGREDIENTS:

Folic acid, DHF+ (B9-Provitamin) . . . . . . . . . . . . . . . . . . . . . . . . . . . . . . . (1.7 mg DFE) 1 mg

Folinic acid (B9-vitamer). . . . . . . . . . . . . . . . . . . . . . . . . . . . . . . . . . . (4.25 mg DFE) 2.5 mg

Levomefolic acid (B9 & B12- cofactor) . . . . . . . . . . . . . . . . . . . . . . . . . . (9 mg DFE) 5.23 mg

Vitamin B12 [cobamamide] . . . . . . . . . . . . . . . . . . . . . . . . . . . . . . . . . . . . . . . . . . .50 mcg^1

FeGC (1.5 mg elemental iron from ferrous glycine cysteinate) . . . . . . . . . . . . 13.6 mg^2,3

INACTIVE INGREDIENT

FUNCTIONAL EXCIPIENTS: 25 mg ascorbates^3,4 (24 mg magnesium l-ascorbate, 1 mg zinc l-ascorbate), 500 mcg betaine (trimethylglycine), flavin adenine dinucleotide^6 (FAD), 1 mg magnesium l-threonate, 25 mcg nicotinamide adenine dinucleotide hydride^6 (NADH), at least 23.33 mg phospholipid-omega 3 complex^5 [marine lipids], 25 mcg pyridoxal 5’ phosphate^6 (P5P), 25 mcg thiamine pyrophosphate^6.

OTHER EXCIPIENTS: Annatto [colorant], citrates (citric, sodium) [stabilizers], gelatin (bovine), glycerine, plant lipids (sunflower) [lecithin], natural orange flavor [masking], piperine [bioavailability enhancer], purified water, ubidecarenone [antioxidant], yellow beeswax.

^1 The form most found in mammalian liver. ^2 Pure amino acid, cysteinated iron chelate. ^3 20% Daily Value (DV) of VITAMIN C, and 5% DV IRON for pregnancy. ^4 NOT a significant source of magnesium and zinc. ^5 Contains at least 12 mg phosphatidylserine (PS) – of which approximately 6.4 mg as PS-DHA-Ca, and less than 1% EPA (<800 mcg PS-EPA-Ca). ^6 Contains less than 2% (<25 mcg/each) of vitamins B1, B2, B3, and B6.

MECHANISM OF ACTION:

Vitamin B12 [TREATMENT]; FOLATE [PREVENTION]; OTHER [SUPPLEMENTATION];

INDICATIONS:

EnBrace HR® is indicated in the TREATMENT of vitamin deficiency - specifically vitamin B12 deficiency, and the PREVENTION of vitamin B12-cofactor deficiency, l-methylfolate.

Requirements of vitamin B9 and/or vitamin B12 in excess of normal due to pregnancy can usually be met with oral supplementation.

PRECAUTIONS:

GENERAL:

0.1 mg or more of folic acid daily may obscure pernicious anemia in that the hematological remission may occur while neurological manifestations remain progressive. The safe tolerable limit for folic acid (in preparations) is 1 mg [emphasis added].

Folic acid is not a substitute for vitamin B12 - although it may improve vitamin B12-deficient megaloblastic anemia. Exclusive use of folic acid in treating vitamin B12-deficient megaloblastic anemia could result in progressive and irreversible neurologic damage. Specifically, vitamin B12 deficiency allowed to progress over 3 months may produce permanent degenerative lesions of the spinal cord - as observed when folate therapy is used as the only hematopoietic agent.

Doses of vitamin B12 exceeding 10 mcg daily may produce hematologic response in patients with folate deficiency. Indiscriminate administration may mask the true diagnosis.

A dietary deficiency of only vitamin B12 is rare; multiple vitamin deficiency is expected in any dietary deficiency. No single regimen fits all cases, and the status of the patient observed in follow-up is the final criterion for adequacy of therapy.

DRUG INTERACTIONS:

Colchicine, para-aminosalicylic acid, and heavy alcohol intake for longer than 2 weeks may produce malabsorption of vitamin B12.

CARCINOGENESIS, MUTAGENESIS, IMPAIRMENT OF FERTILITY:

There is no evidence from long-term use in patients with pernicious anemia that vitamin B12 or folate is carcinogenic. Pernicious anemia is associated with increased incidence of carcinoma of the stomach, but this is believed to be related to the underlying pathology and not to treatment with vitamin B12.

PREGNANCY, NURSING MOTHERS, PEDIATRIC USE:

Vitamin B9 and vitamin B12 are essential vitamins and requirements are increased during pregnancy. Amounts of vitamin B9 and vitamin B12 that are recommended by the Food and Nutrition Board, National Academy of Science - National Research Council for lactating women should be consumed during pregnancy.

Vitamin B12 and vitamin B9 appear in the milk of nursing mothers in concentrations which approximate the mother’s vitamin B12 and vitamin B9 blood level. Amounts of vitamin B12 that are recommended by the Food and Nutrition Board, National Academies of Science - National Research Council for lactating women should be consumed during lactation.

Intake in pediatric patients should be in the amount recommended by the Food and Nutrition Board, National Academy of Science - National Research Council.

ADVERSE REACTIONS:

Mild transient diarrhea, polycythemia vera, itching, transitory exanthema, feeling of swelling of entire body may occur with administration of vitamin B12.

Allergic sensitization has been reported following both oral and parenteral administration of folic acid.

DOSAGE AND ADMINISTRATION:

The recommended dosage is one (1) capsule daily, preferably on an empty stomach. Dosage may be adjusted by a healthcare provider based on individual patient needs.

As a general rule reticulocyte plasma count, folate and vitamin B12 status must be obtained prior to treatment.

Do not exceed the recommended dose. Call your medical practitioner about side effects. You may report side effects by calling (866) 280-5961.

HOW SUPPLIED:

Oval, brownish-orange softgel capsule with imprint ENL.

STORAGE:

Store at 20°-25°C (68°-77°F). Protect from light and moisture.

Rx ONLY

KEEP OUT OF THE REACH OF CHILDREN.

Tamper-Evident: Do not use if the seal is broken or missing.

MANUFACTURED FOR:

JayMac Pharmaceuticals, LLC; Sunset, LA 70584.

MANUFACTURED IN INDIA / PACKAGED IN USA

PATENTS:

Patent applications pending.

TRADEMARKS:

EnBrace HR® is a registered mark of JayMac Pharmaceuticals. DeltaFolate™ is a use-trademark of JayMac Pharmaceuticals.

Revision (February 4, 2026)

PRINCIPAL DISPLAY PANEL:

EnBrace HR ®

with DeltaFolateTM

NDC 64661-650-30

Rx Only

[15 mg DFE Folate] [50 mcg CBI][1.5 MG FeGC]

ANTI-ANEMIA PREPARATION

Low-IRON

JayMac Pharmaceuticals, LLC

SOFTGEL (30 ct BOTTLE)

Prescription Prenatal Vitamin For Therapeutic Use